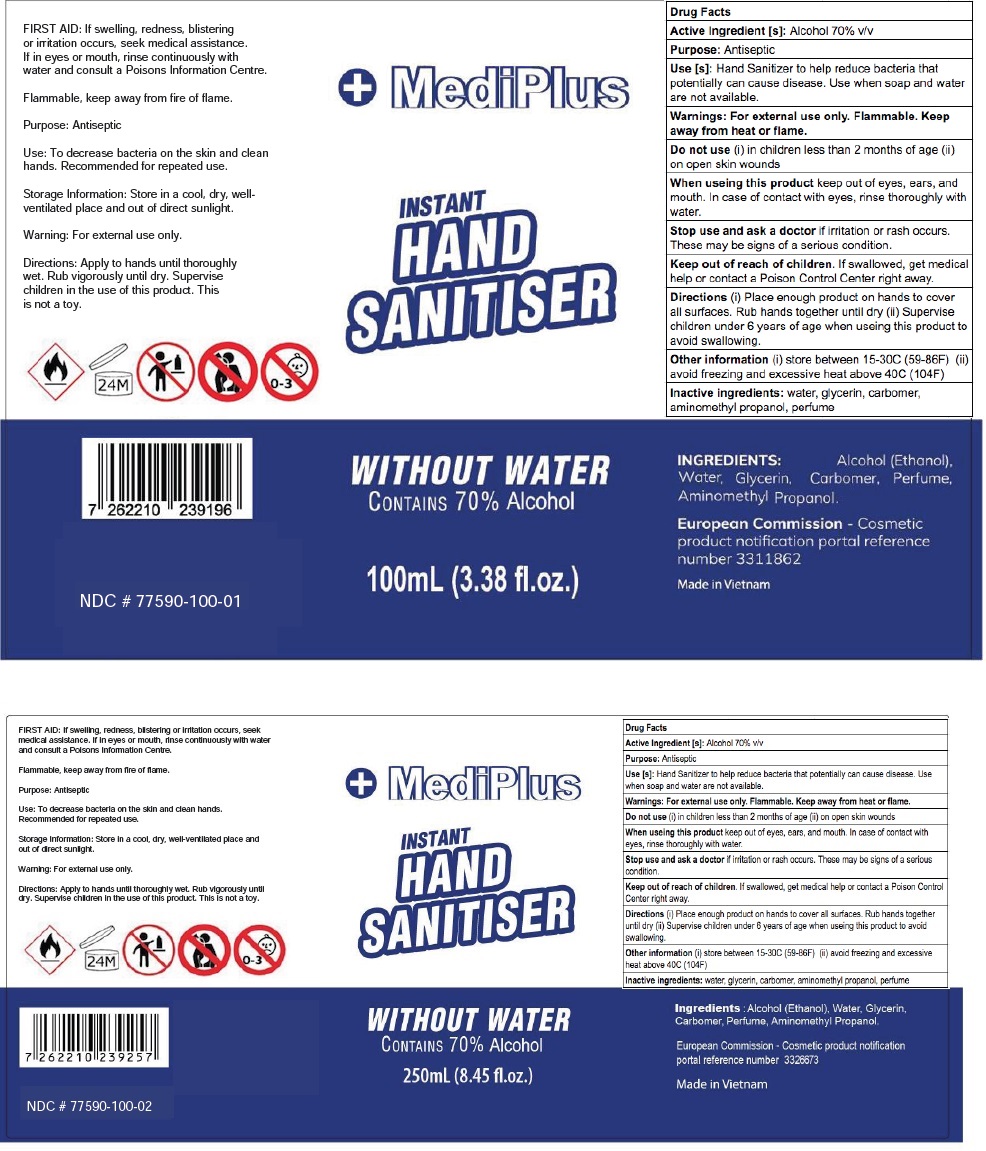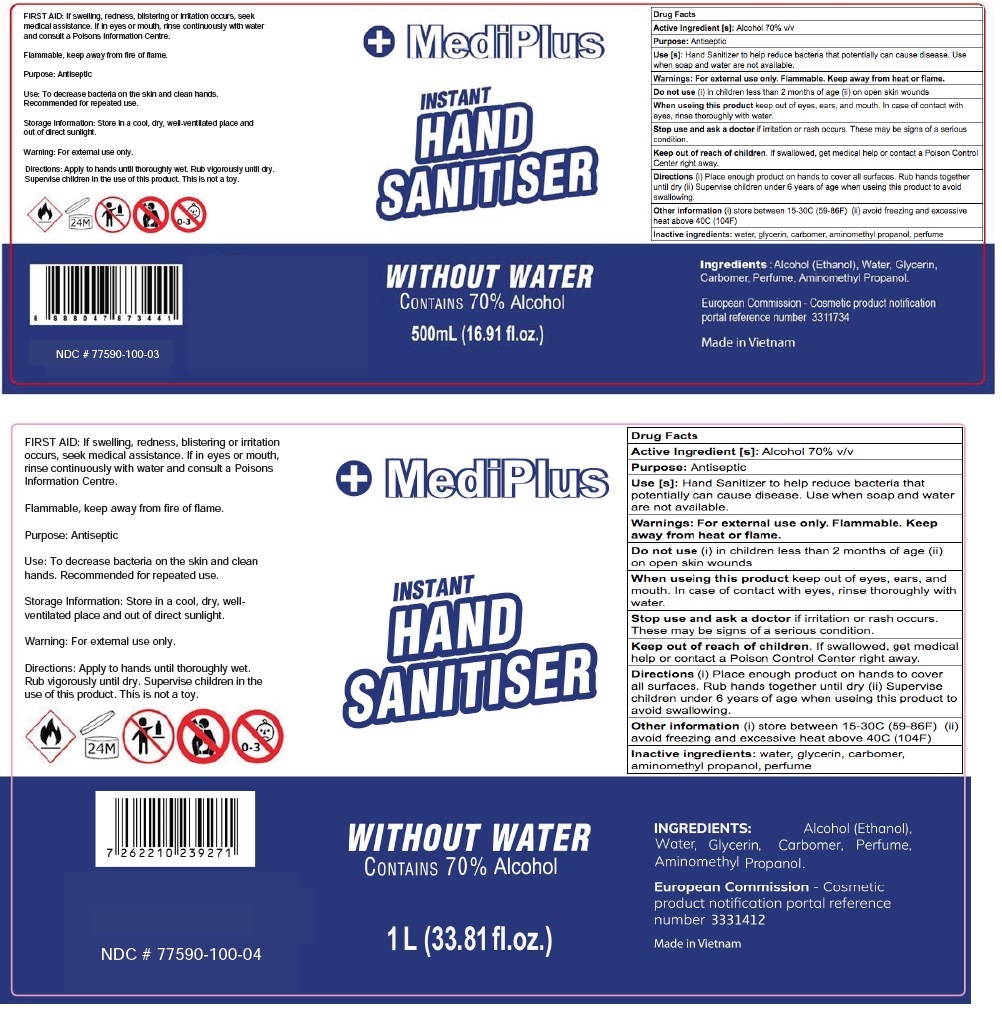 DRUG LABEL: MEDIPLUS
NDC: 77590-100 | Form: LIQUID
Manufacturer: Spartan Bizcorp Pte. Ltd.
Category: otc | Type: HUMAN OTC DRUG LABEL
Date: 20200518

ACTIVE INGREDIENTS: ALCOHOL 70 mL/100 mL
INACTIVE INGREDIENTS: WATER; GLYCERIN; CARBOMER HOMOPOLYMER, UNSPECIFIED TYPE; AMINOMETHYLPROPANOL

MediPlus INSTANT HAND SANITIZER

Active Ingredient [s]: Alcohol 70% v/v

Purpose: Antiseptic

INDICATIONS AND USAGE

Use [s]: Hand Sanitizer to help reduce bacteria that potentially can cause disease. Use when soap and water are not available.

WARNINGS

Warnings : For external use only. Flammable. Keep away from heat or flame.

Do not use (i) in children less than 2 months of age (ii) on open skin wounds

When using this product keep out of eyes, ears, and mouth. In case of contact with eyes, rinse thoroughly with water.

Stop use and ask a doctor if irritation or rash occurs. These may be signs of a serious condition.

Keep out of reach of children. If swallowed, get medical help or contact a Poison Control Center right away.

DOSAGE AND ADMINISTRATION

Directions (i) Place enough product on hands to cover all surfaces. Rub hands together until dry

(ii) Supervise children under 6 years of age when using this product to avoid swallowing.

Other information (i) store between 15-30C (59-86F) (ii) avoid freezing and excessive heat above 40C (104F)

INACTIVE INGREDIENT

Inactive ingredients: water, glycerin, carbomer, aminomethyl propanol, perfume

WITHOUT WATER

CONTAINS 70% Alcohol

FIRST AID: If swelling, redness, blistering or irritation occurs, seek medical assistance. If in eyes or mouth, rinse continuously with water and consult a doctor or Poisons Information Centre.

Flammable, keep away from fire or flame.

Purpose: Antiseptic

Use: To decrease bacteria on the skin and clean hands. Recommended for repeated use.

Storage information: Store in a cool, dry, well-ventilated place and out of direct sunlight.

Warning: For external use only.

Directions: Apply to hands until thoroughly wet. Rub vigorously until dry. Supervise children in the use of this product. This is not a toy.

European Commission - Cosmetic product notification portal reference number 3311734

Made in Vietnam